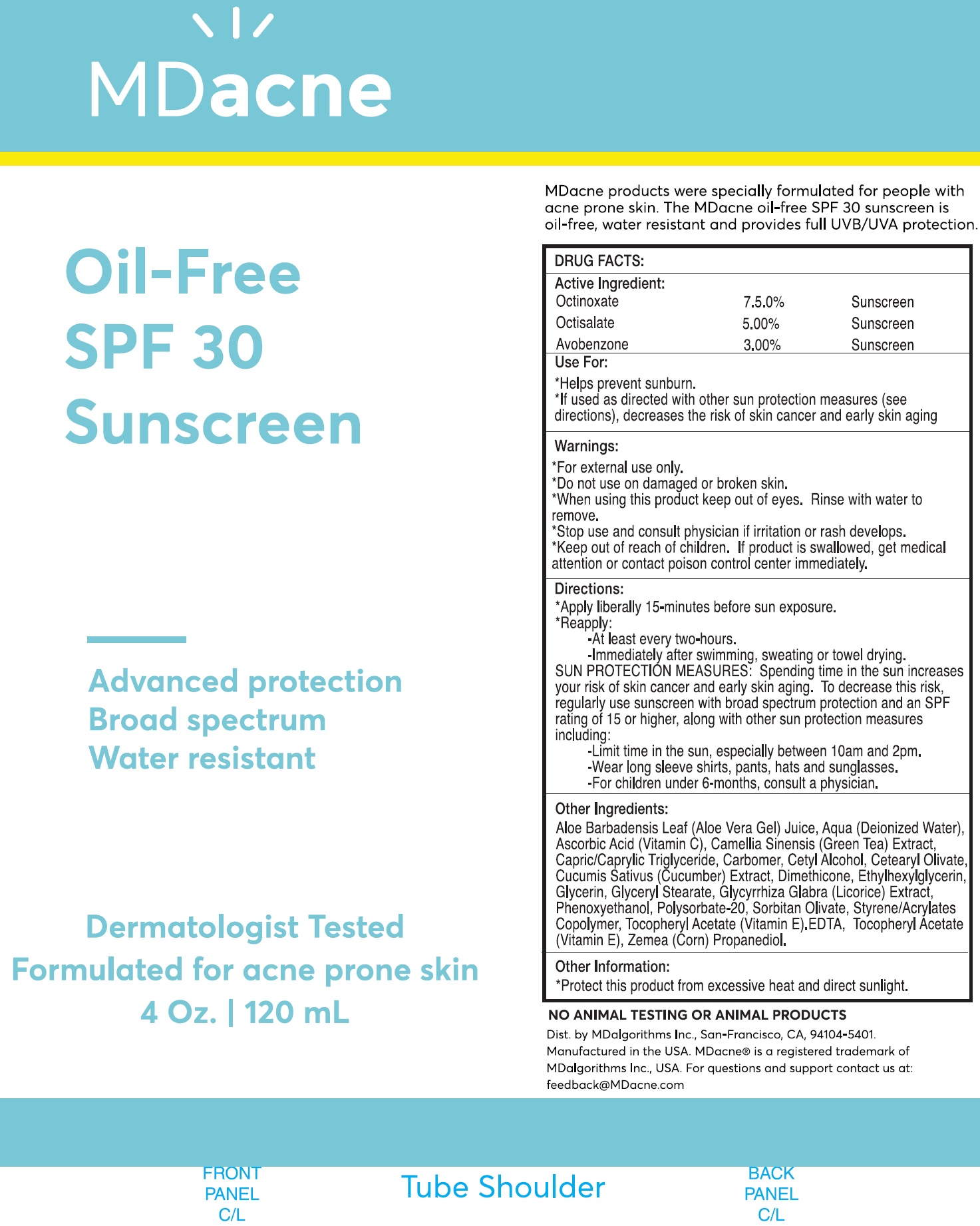 DRUG LABEL: MD Acne Oil Free SPF 30 Sunscreen
NDC: 71804-232 | Form: CREAM
Manufacturer: MD Algorithms Inc.
Category: otc | Type: HUMAN OTC DRUG LABEL
Date: 20231111

ACTIVE INGREDIENTS: OCTINOXATE 75 mg/1 mL; OCTISALATE 50 mg/1 mL; AVOBENZONE 30 mg/1 mL
INACTIVE INGREDIENTS: ALOE VERA LEAF; WATER; ASCORBIC ACID; GREEN TEA LEAF; CARBOXYPOLYMETHYLENE; CETYL ALCOHOL; CETEARYL OLIVATE; CUCUMBER; DIMETHICONE; ETHYLHEXYLGLYCERIN; GLYCERIN; GLYCERYL MONOSTEARATE; LICORICE; PHENOXYETHANOL; POLYSORBATE 20; SORBITAN OLIVATE; .ALPHA.-TOCOPHEROL ACETATE; CORN

MD-Acne Oil-Free SPF-30 Sunscreen

Active Ingredient:

Octinoxate 7.5.0%

Octisalate 5.00%

Avobenzone 3.00%

PURPOSE

Sunscreen

Use For:

- Helps prevent sunburn.
- If used as directed with other sun protection measures (see directions), decreases the risk of skin cancer and early skin aging

Warnings:

- For external use only.

Do not use

- on damaged or broken skin.

When using this product

keep out of eyes. Rinse with water to remove.

Stop use and consult physician

If irritation or rash develops.

Keep out of reach of children.

If product is swallowed, get medical attention or contact poison control center immediately.

Directions:

- Apply liberally 15-minutes before sun exposure.
- Reapply:

- At least every two-hours.

- Immediately after swimming, sweating or towel drying.

SUN PROTECTION MEASURES: Spending time in the sun increases your risk of skin cancer and early skin aging. To decrease this risk, regularly use sunscreen with broad spectrum protection and an SPF rating of 15 or higher, along with other sun protection measures including:

- Limit time in the sun, especially between 10 am and 2 pm.

- Wear long sleeve shirts, pants, hats and sunglasses.

- For children under 6-months, consult a physician.

Other Ingredients:

Aloe Barbadensis Leaf (Aloe Vera Gel) Juice, Aqua (Deionized Water), Ascorbic Acid (Vitamin C), Camellia Sinensis (Green Tea) Extract, Capric/Caprylic Triglyceride, Carbomer, Cetyl Alcohol, Cetearyl Olivate, Cucumis Sativus (Cucumber) Extract, Dimethicone, Ethylhexylglycerin, Glycerin, Glyceryl Stearate, Glycyrrhiza Glabra (Licorice) Extract, Phenoxyethanol, Polysorbate-20, Sorbitan Olivate, Styrene/Acrylates Copolymer, Tocopheryl Acetate (Vitamin E).EDTA, Tocopheryl Acetate (Vitamin E), Zemea (Corn) Propanediol.

Other Information:

- Protect this product from excessive heat and direct sunlight.